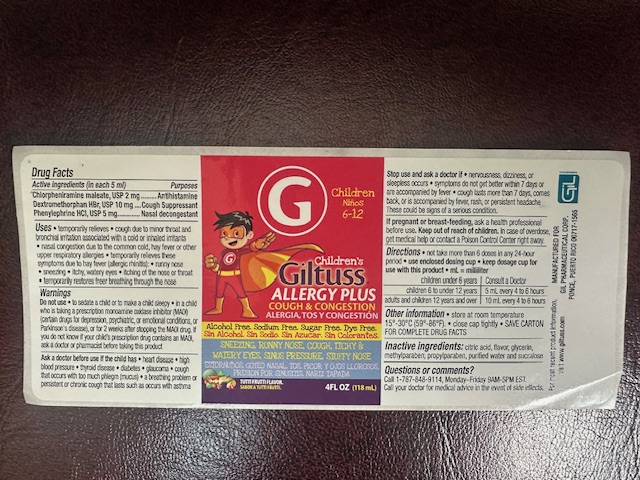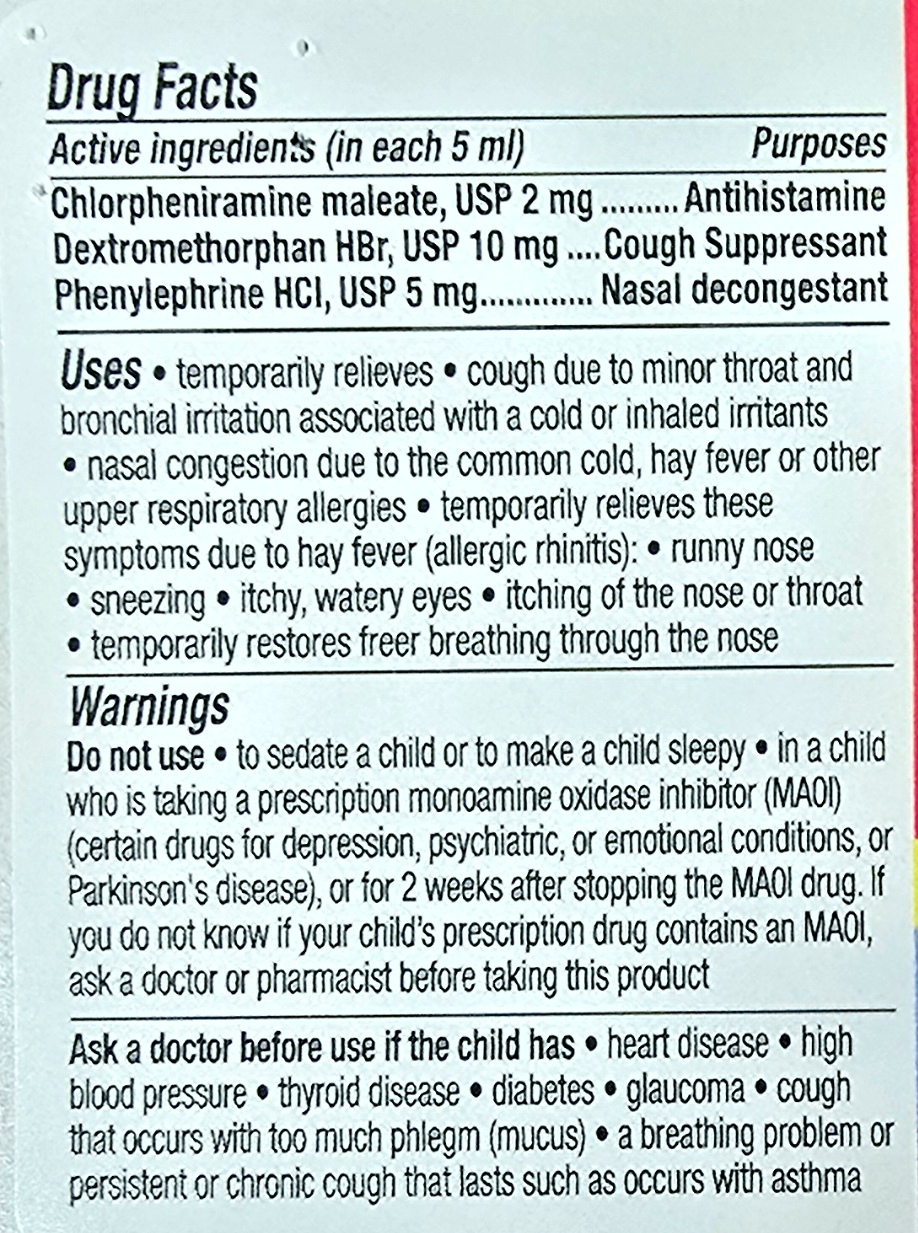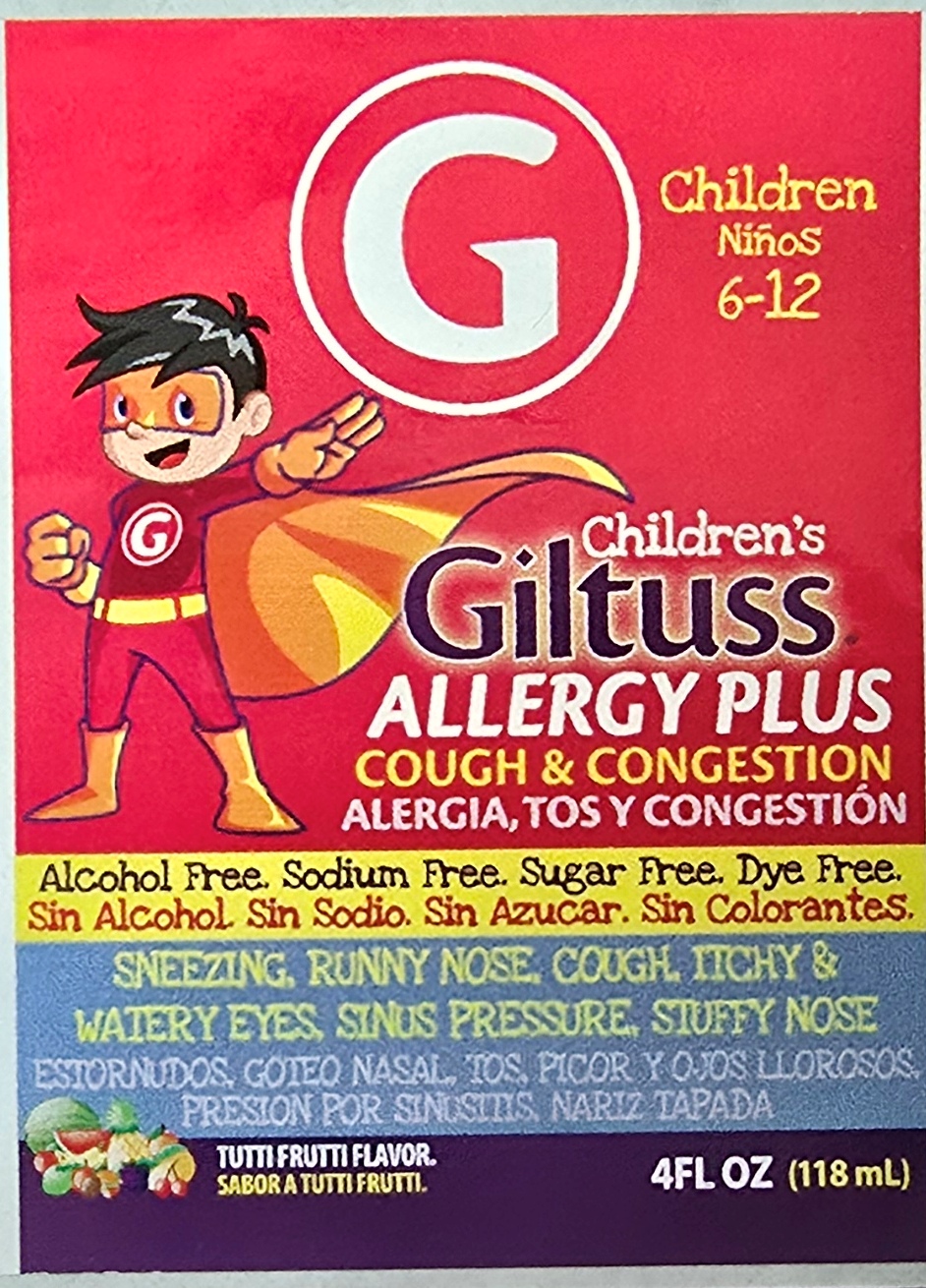 DRUG LABEL: Giltuss Childrens Allergy Plus
NDC: 65852-018 | Form: SOLUTION
Manufacturer: Dextrum Laboratories Inc.
Category: otc | Type: HUMAN OTC DRUG LABEL
Date: 20250925

ACTIVE INGREDIENTS: PHENYLEPHRINE HYDROCHLORIDE 5 mg/5 mL; CHLORPHENIRAMINE MALEATE 2 mg/5 mL; DEXTROMETHORPHAN HYDROBROMIDE 10 mg/5 mL
INACTIVE INGREDIENTS: CITRIC ACID; METHYLPARABEN; PROPYLPARABEN; WATER; SUCRALOSE; GLYCERIN

Children's Giltuss Allergy Plus

Active Ingredients

Active Ingredients (in each 5 mL) Purpose

Chlorpheniramine maleate, USP 2 mg ------------------Antihistamine

Dextromethorphan HBr, USP 10 mg -----------------------Cough supressant

Phenylephrine HCl, USP 5 mg -------------------------------Nasal decongestant

indication and usage section

Not take more than 6 doses in any 24-hour period

Use enclosed dosing cup

Keep dosage cup for use this product

ML=Milliliter

Children undre 6 years, consult the doctor

Children 6 to under 12 years, 5 ml every 4 to 6 hours

Adults and children 12 years and over, 10 ml every 4 to 6 hours

Keep out of reach of children section

In case of overdose, get medical help or contact a Poison Control Center right away.

Inactive ingredient section

Citric acid, flavor, glycerin, metylparaben, propylparaben, purified water, and sucralose.

Purpose section

Antihistamine

Cough Suppressant

Nasal Descongestant

Question section

Call 1-787-848-9114, Monday-Friday 9AM-5PM EST.

Call your doctor for medical advice in the event of side effects

Warnings Section

Do not use to sedate a child or to makea child sleepy

in a child who is taking a prescription monoamine oxidase inhibitor(MAOI)(certain drugs for depression, psychiatric, or emotional condition, or Parkingson's disease), or for 2 weeks after stopping the MAOI drug.

If you do not know if your child's prescription drug contains a MAOI, ask a doctor or pharmacistbefore taking this products.

Dosage and administration section

Not take more than 6 doses in any 24-hour period

Use enclosed dosing cup

Keep dosage cup for use this product

ML=Milliliter

Children undre 6 years, consult the doctor

Children 6 to under 12 years, 5 ml every 4 to 6 hours

Adults and children 12 years and over, 10 ml every 4 to 6 hours

PACKAGE LABEL

Principal panel

Children 6-12

Children's Giltuss Allergy Plus

Cough & Congestion

Alcohol free, Sodium free, Sugar free,Dye free

Sneezing, runny nose, cough, itchy & watery eyes, sinus pressure, stuffy nose

Tutti Frutti flavor

4 floz (118 mL)